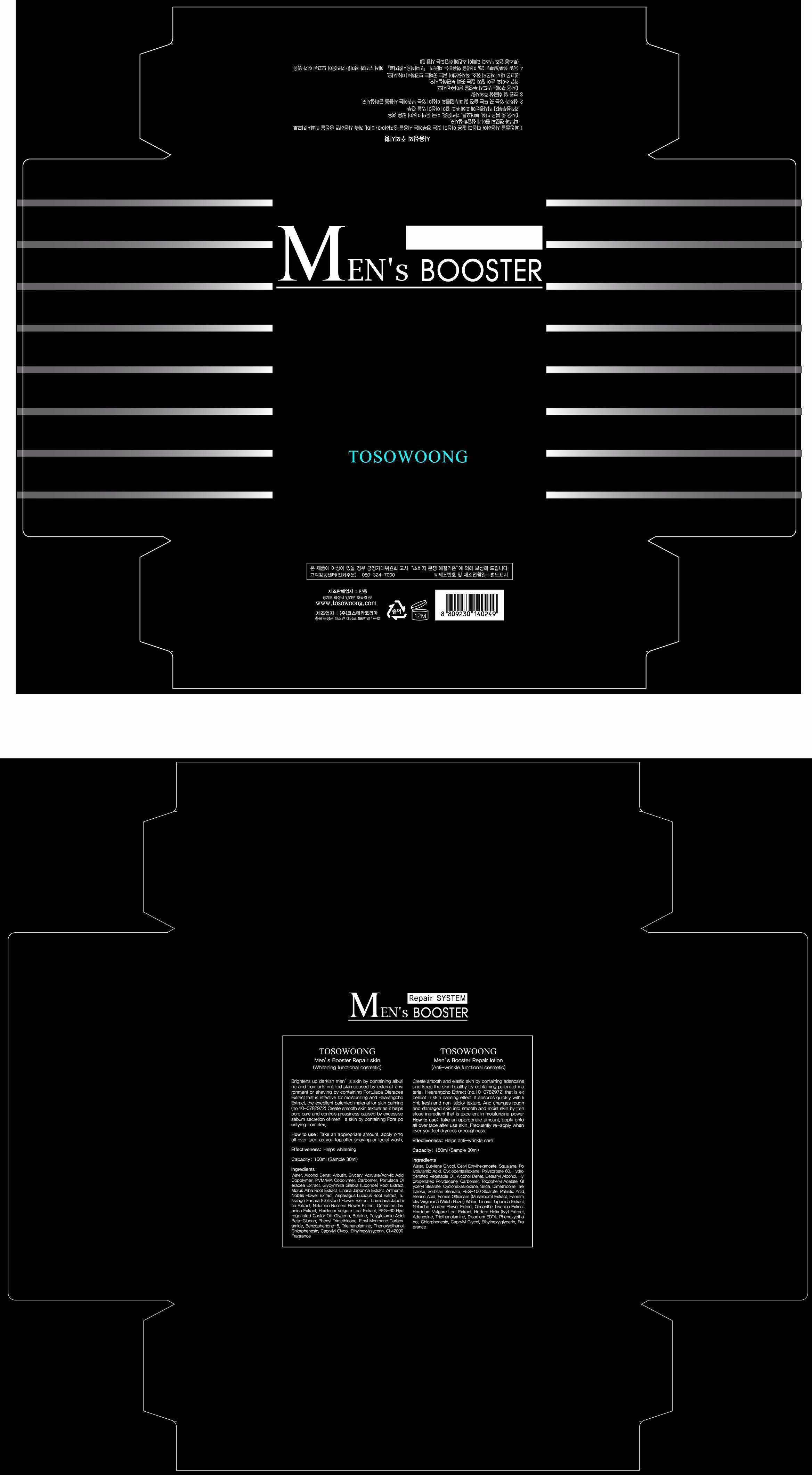 DRUG LABEL: Tosowoong Mens Booster Repair Skin
NDC: 55249-1001 | Form: LIQUID
Manufacturer: Mantong
Category: otc | Type: HUMAN OTC DRUG LABEL
Date: 20130705

ACTIVE INGREDIENTS: ARBUTIN 1 mg/150 mL
INACTIVE INGREDIENTS: WATER; ALCOHOL; PORTULACA OLERACEA WHOLE; GLYCYRRHIZA GLABRA; MORUS ALBA ROOT BARK; CHAMAEMELUM NOBILE FLOWER; ASPARAGUS COCHINCHINENSIS TUBER; PETASITES FRAGRANS; NELUMBO NUCIFERA FLOWER; BARLEY; POLYOXYL 60 HYDROGENATED CASTOR OIL; GLYCERIN; BETAINE; PHENYL TRIMETHICONE; ETHYL MENTHANE CARBOXAMIDE; BENZOPHENONE-5; PHENOXYETHANOL; CHLORPHENESIN

Drug Facts

ACTIVE INGREDIENT

arbutin

INACTIVE INGREDIENT

water, alcohol, glyceryl acrylate/acrylic acid copolymer, PVM/MA copolymer, carbomer, portulaca oleracea extract, licorice root extract, morus alba root extract, linaria japonica extract, anthemis nobilis flower extract, asparagus lucidus root extract, coltsfood flower extract, laminaria japonica extract, nelumbo nucifera flower extract, oenanthe javanica extract, hordeum vulgare leaf extract, PEG=60 hydrogenated castor oil, glycerin, betaine, polyglutamic acid, beta-glucan, phenyl trimethicone, ethyl menthane carboxamide, benzophenone-5, triethanolamine, phenoxyethanol, chlorphenesin, caprylyl glycol, ethylhexylglycerin, CI 42090, fragrance

PURPOSE

helps skin whitening

keep out or reach of the children

INDICATIONS AND USAGE

take appropriate amount and apply onto all over face after shaving or facial wash

WARNINGS

avoid contact with eyes

DOSAGE AND ADMINISTRATION

for external use only